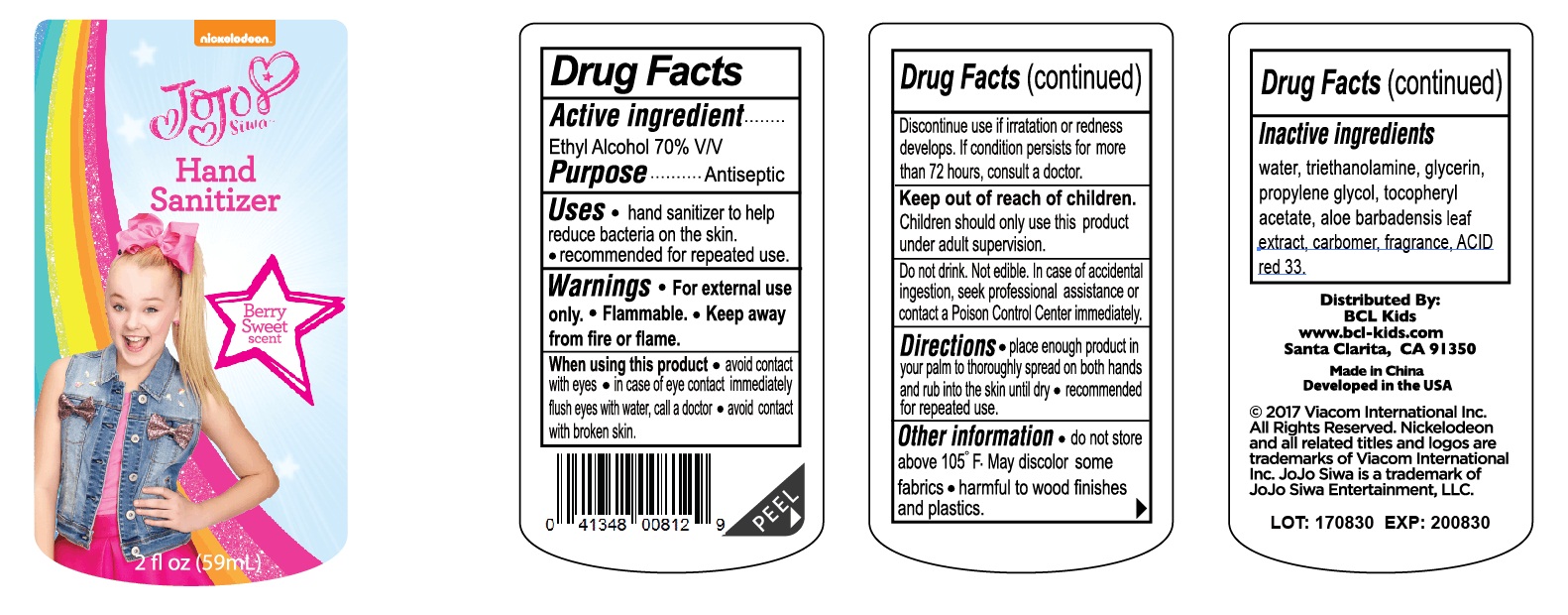 DRUG LABEL: nickelodeon jojo siwa hand sanitizer
NDC: 40104-289 | Form: GEL
Manufacturer: Ningbo Pulisi Daily Chemical Products Co., Ltd.
Category: otc | Type: HUMAN OTC DRUG LABEL
Date: 20170929

ACTIVE INGREDIENTS: alcohol 70 mL/100 mL
INACTIVE INGREDIENTS: WATER; PROPYLENE GLYCOL; ALOE VERA LEAF; GLYCERIN; .ALPHA.-TOCOPHEROL ACETATE; TROLAMINE

Drug facts

Active ingredient Purpose

Ethyl Alcohol 70% ... Antiseptic

PURPOSE

Hand sanitizer to help reduce bacteria on the skin.

KEEP OUT OF REACH OF CHILDREN

Do not drink, Not edible. In case of accidental ingestion, seek professional assistance or contact local poison control center right away.

Children should be only use this product under adult supervised.

INDICATIONS AND USAGE

aviud contact with eyes;

in case of eye contact immediately flush eyes with water, call a doctor;

avoid contact with broken skin.

WARNINGS

For external use only.
Flammable. Keep away from hear or flame.

Discontinue use, if irritation and redness develops, if condition persists for more than 72 hours, consult a doctor.

DOSAGE AND ADMINISTRATION

place enough product in your palms to thoroughly spread on both hands, and rub the skin until dry.

recommended for repeated use.

INACTIVE INGREDIENT

Water, Carbomer, Glycerin, Propylene Glycol, Triethanolamine, Aloe Barbadensis Leaf extract, Tocopheryl Acetate, Fragrance, acid red 33